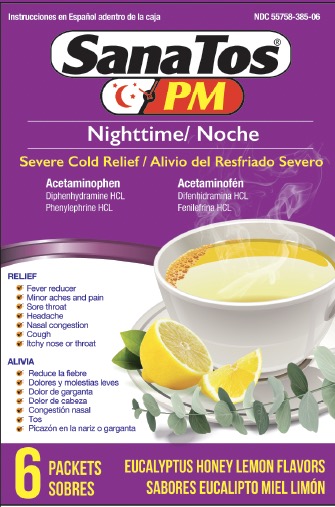 DRUG LABEL: SanaTos
NDC: 55758-385 | Form: GRANULE, FOR SOLUTION
Manufacturer: Pharmadel LLC
Category: otc | Type: HUMAN OTC DRUG LABEL
Date: 20260115

ACTIVE INGREDIENTS: DIPHENHYDRAMINE HYDROCHLORIDE 25 mg/1 1; PHENYLEPHRINE HYDROCHLORIDE 10 mg/1 1; ACETAMINOPHEN 650 mg/1 1
INACTIVE INGREDIENTS: ISOPROPYL ALCOHOL; WATER; ACESULFAME POTASSIUM; ASPARTAME; ANHYDROUS CITRIC ACID; D&C YELLOW NO. 10; FD&C BLUE NO. 1; FD&C RED NO. 40; MALTODEXTRIN; SILICON DIOXIDE; SODIUM CITRATE; SUCROSE; TRIBASIC CALCIUM PHOSPHATE

SanaTos Nighttime EHL Powder (AS)

Drug Facts

Active ingredients & Purposes

PURPOSE

Active Ingredients (in each packet) | Purposes
Acetaminophen 650 mg | Pain reliever/ fever reducer
Diphenhydramine HCL 25 mg | Antihistamine/ cough suppressant
Phenylephrine HCL 10 mg | Nasal decongestant

Uses

Temporarily relieves common cold/flu symptoms:

- minor aches and pains
- sore throat
- headache
- nasal congestion
- runny nose
- itchy nose and throat
- cough due to minor throat & bronchial irritation
- and temporarily reduces fever

Warnings

Liver warning: This product contains acetaminophen. Severe liver damage may occur if you take

- more than 6 doses in 24 hours, which is the maximum daily amount
- with other drugs containing acetaminophen
- 3 or more alcoholic drinks every day while using this product

Allergy alert: Acetaminophen may cause severe skin reactions. Symptoms may include: 

- skin reddening
- blisters
- rash. If a skin reaction occurs, stop use and seek medical help right away.

Sore throat warning: if sore throat is severe, persists for more than 2 days, is accompanied or followed by fever, headache, rash, nausea, or vomiting, consult a doctor promptly.

Do not use

- with any other drug containing acetaminophen (prescription or nonprescription). If you are not sure whether a drug contains acetaminophen, ask a doctor or pharmacist.
- if you are now taking a prescription monoamine oxidase inhibitor (MAOI) (certain drugs for depression, psychiatric or emotional conditions, or Parkinson's disease), or for 2 weeks after stopping the MAOI drug. If you do not know if your prescription drug contains an MAOI, ask a doctor or pharmacist before taking this product.
- with any other product containing diphenhydramine, even one used on skin

Ask a doctor before use if you

- have liver disease
- have heart disease
- have high blood pressure
- have thyroid disease
- have diabetes
- have glaucoma
- have a breathing problem such as emphysema
- have difficulty urinating due to an enlarged prostate gland
- have a breathing problem such as emphysema or chronic bronchitis
- are taking sedatives or tranquilizers

Ask a doctor or pharmacist before use if you are

- taking the blood thinning drug warfarin

When using this product

- do not exceed recommended dosage

- may cause excitability, especially in children
- use caution when driving a motor vehicle or operating machinery
- may cause marked drowsiness

Stop use and ask doctor if

- nervousness, dizziness, or sleeplessness occur
- redness or swelling is present
- pain, cough, or nasal congestion persists or gets worse or last more than 7 days
- fever gets worse or lasts more than 3 days
- any new symptoms occur
- cough comes back or occurs with rash or headache that lasts. These could be signs of a serious condition.

If pregnant or breast-feeding,

ask a health professional before use.

Kepp out of reach of children.

In case of accidental overdose, get medical help or contact a Poison Control Center right away. Prompt medical attention is critical for adults as well as for children even if you do not notice any signs or symptoms.

Directions

- dissolve one packet in an 8 fl oz glass of hot water. If using a microwave; add content into a glass of cool water and stir briskly before and after heating. Do not overheat.
- Sip while hot and consume the entire drink within 10-15 minutes
- adults and children 12 years of age and older: one (1) packet every 4 hours, do not exceed 6 packets per 24 hours
- children under 12 years of age: do not use

Other information

- each packet contains: potassium 10 mg, sodium 27 mg
- phenylketonurics: contains phenylalanine 13 mg per packet
- store at room temperature 68-77°F (20-25°C)
- do not use if packets are punctured or torn.

Inactive ingredients

acesulfame potassium, anhydrous citric acid, aspartame, D&C yellow #10, eucalyptus honey lemon flavors, FD&C blue #1, FD&C red #40, isopropyl alcohol, maltodextrin, silicon dioxide, sodium citrate, sucrose, tribasic calcium phosphate, water

Questions?

+1-866-359-3478 (M-F) 9 AM to 5 PM EST or www.pharmadel.com

Distributed by:

PHARMADEL LC

New Castle, DE 19720

Made in India